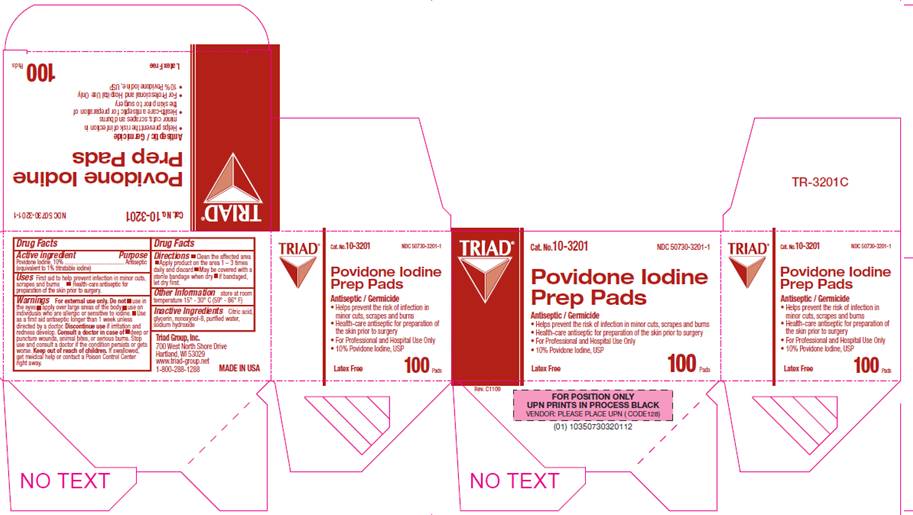 DRUG LABEL: Povidone Iodine Prep Pad
NDC: 50730-3201 | Form: SOLUTION
Manufacturer: H and P Industries, Inc. dba Triad Group
Category: otc | Type: HUMAN OTC DRUG LABEL
Date: 20091201

ACTIVE INGREDIENTS: povidone-iodine .10 g/1 1
INACTIVE INGREDIENTS: citric acid monohydrate; glycerin; sodium hydroxide; water

DRUG FACTS

ACTIVE INGREDIENT

Povidone Iodine 10% w/v (equivalent to 1% titratable iodine)

PURPOSE

Antiseptic

USES

- First Aid Antiseptic to help prevent infection in minor cuts, scrapes and burns
- Health Care Antiseptic for preparation of the skin prior to surgery

WARNINGS

For external use only.

Do not use

- in the eyes
- apply over large areas of the body
- use on individuals who are allergic or sensitive to iodine
- use as a first aid antiseptic for longer than 1 week unless directed by a doctor

Ask a doctor in case of

- deep or puncture wounds
- animal bites
- serious burns

Stop use and ask a doctor

- if condition persists for more than 72 hours
- if irritation and redness develop

Keep out of reach of children

If swallowed, get medical help or contact a Poison Control Center right away.

DIRECTIONS

- clean the affected area
- apply a small amount of this product to the area 1-3 times daily and discard
- may be covered with a sterile bandage when dry

OTHER INFORMATION

Store at room temperature 15° - 30° C (59° - 86° F)

INACTIVE INGREDIENTS

citric acid, glycerin, nonoxynol-8, purified water, sodium hydroxide

PACKAGE INFORMATION

Triad
Cat. No. 10-3201
NDC 50730-3201-1
Povidone Iodine
Prep Pads
Antiseptic / Germicide

- Helps prevent the risk of infection in minor cuts, scrapes and burns
- Health-care antiseptic for preparation of the skin prior to surgery
- For Professional and Hospital Use Only
- 10% Povidone Iodine, USP

Latex Free
100 Pads
Triad Group, Inc.
700 West North Shore Drive
Hartland, WI 53029
www.triad-group.net
1-800-288-1288
MADE IN USA